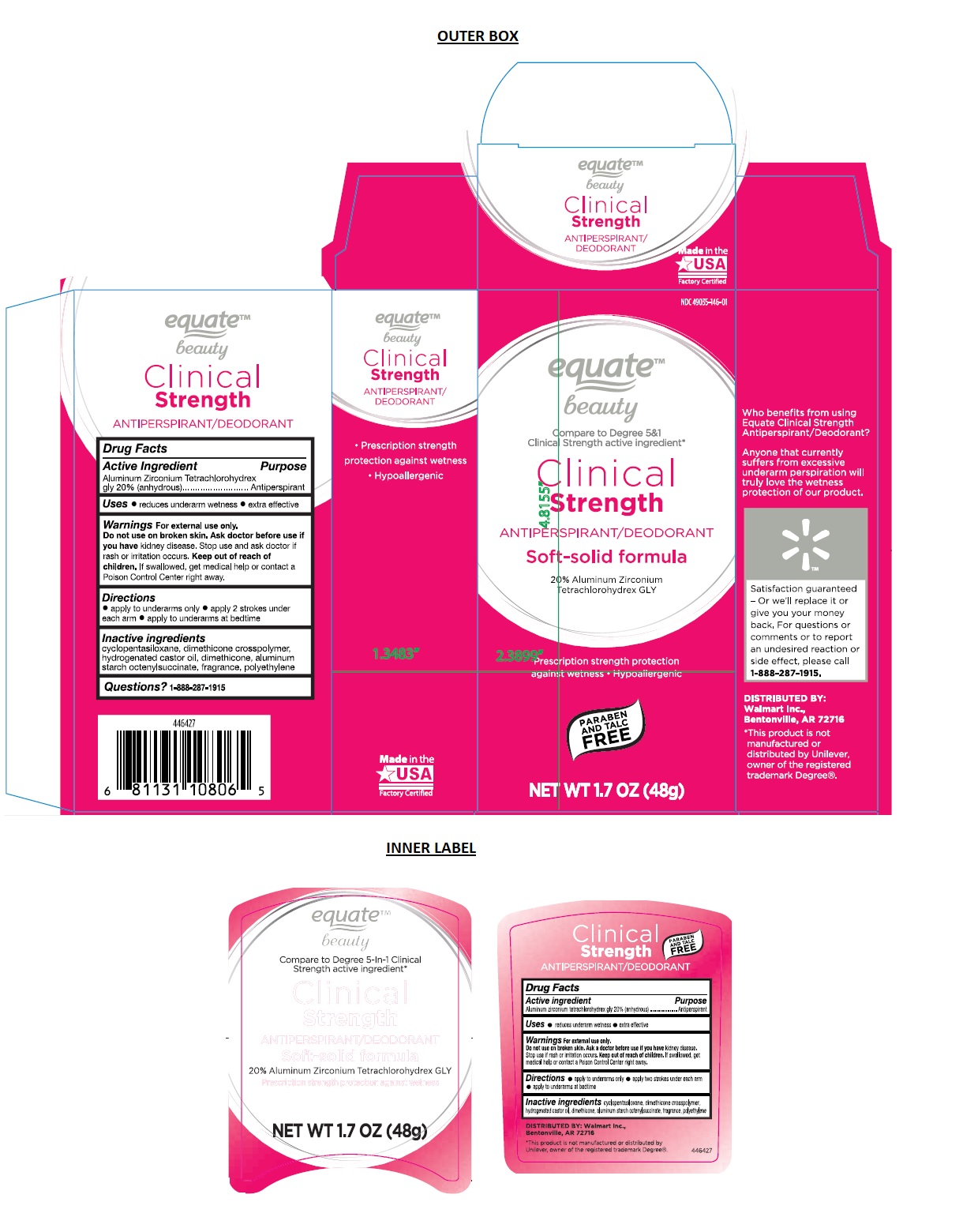 DRUG LABEL: equate ANTIPERSPIRANT
NDC: 49035-146 | Form: STICK
Manufacturer: Wal-mart Stores, Inc.
Category: otc | Type: HUMAN OTC DRUG LABEL
Date: 20181022

ACTIVE INGREDIENTS: ALUMINUM ZIRCONIUM TETRACHLOROHYDREX GLY 0.2 g/1 g
INACTIVE INGREDIENTS: CYCLOMETHICONE 5; DIMETHICONE CROSSPOLYMER (450000 MPA.S AT 12% IN CYCLOPENTASILOXANE); HYDROGENATED CASTOR OIL; DIMETHICONE; ALUMINUM STARCH OCTENYLSUCCINATE; LOW DENSITY POLYETHYLENE

Equate ANTIPERSPIRANT

Active Ingredient

Aluminum Zirconium Tetrachlorohydrex gly 20% (anhydrous)

Purpose

Antiperspirant

Uses

• reduces underarm wetness • extra effective

Warnings

For external use only.

Do not use on broken skin. Ask doctor before use if you have kidney disease. Stop use and ask doctor if rash or irritation occurs.

Keep out of reach of children. If swallowed, get medical help or contact a Poison Control Center right away.

Directions

• apply to underarms only • apply 2 strokes under each arm • apply to underarms at bedtime

Inactive ingredients

cyclopentasiloxane, dimethicone crosspolymer, hydrogenated castor oil, dimethicone, aluminum starch octenylsuccinate, fragrance, polyethylene

Compare to Degree 5 &1 Clinical Strength Active Ingredient*

Clinical Strength

ANTIPERISPERANT/DEODORANT

Soft-Solid formula

Prescription strength protection against wetness

Hypoallergenic

PARABEN AND TALC FREE

20% aluminum zirconium tetrachlorohydrex GLY

Distributed by: Wal-Mart Stores, Inc., Bentonville, AR 72716, © Wal-Mart Stores, Inc.

*This product is not manufactured by Unilever, owner of the registered trademark Degree®. GN